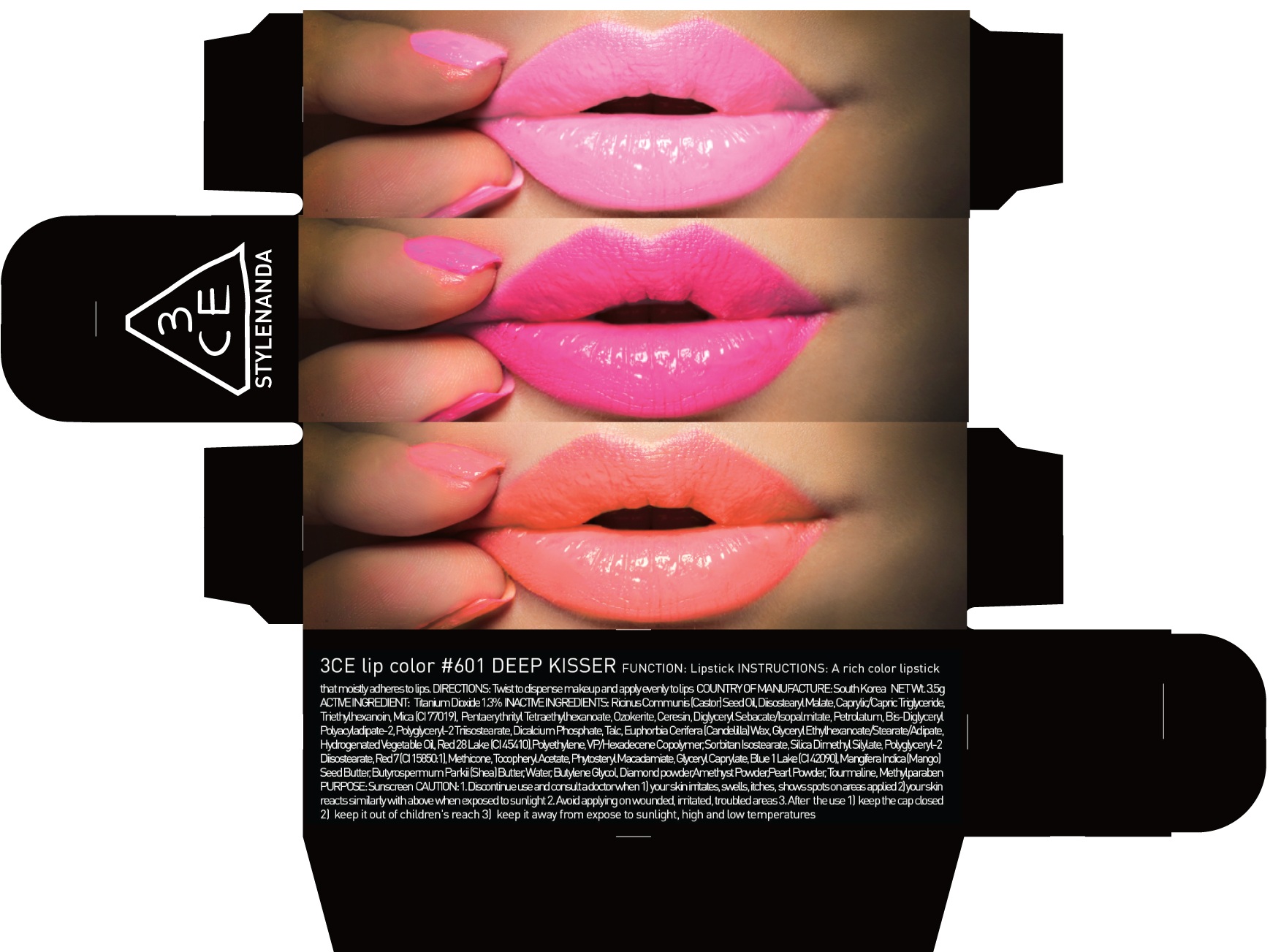 DRUG LABEL: 3CE LIP COLOR 601 DEEP KISSER
NDC: 60764-078 | Form: LIPSTICK
Manufacturer: Nanda Co., Ltd
Category: otc | Type: HUMAN OTC DRUG LABEL
Date: 20161007

ACTIVE INGREDIENTS: Titanium Dioxide 0.04 g/3.5 g
INACTIVE INGREDIENTS: Diisostearyl Malate; Triethylhexanoin

ACTIVE INGREDIENT

Active Ingredient: Titanium Dioxide 1.3%

INACTIVE INGREDIENT

Inactive Ingredients: RicinusCommunis (Castor) Seed Oil, Diisostearyl Malate, Caprylic/Capric Triglyceride, Triethylhexanoin, Mica (CI 77019), PentaerythritylTetraethylhexanoate, Ozokerite, Ceresin, DiglycerylSebacate/Isopalmitate, Petrolatum, Bis-Diglyceryl Polyacyladipate-2, Polyglyceryl-2 Triisostearate, Dicalcium Phosphate, Talc, Euphorbia Cerifera (Candelilla) Wax, Glyceryl Ethylhexanoate/Stearate/Adipate, Hydrogenated Vegetable Oil, Red 28 Lake (CI 45410), Polyethylene, VP/Hexadecene Copolymer, SorbitanIsostearate, Silica Dimethyl Silylate, Polyglyceryl-2 Diisostearate, Red 7 (CI 15850:1), Methicone, Tocopheryl Acetate, PhytosterylMacadamiate, Glyceryl Caprylate, Blue 1 Lake (CI 42090), MangiferaIndica (Mango) Seed Butter, ButyrospermumParkii (Shea) Butter, Water, Butylene Glycol, Diamond powder, Amethyst Powder, Pearl Powder, Tourmaline, Methylparaben

PURPOSE

Purpose: Sunscreen

CAUTION

CAUTION: 1. Discontinue use and consult a doctor when - your skin irritates, swells, itches, shows spots on areas applied - your skin reacts similarly with above when exposed to sunlight 2. Avoid applying on wounded, irritated, troubled areas 3. After the use - keep the cap closed - keep it out of children's reach - keep it away from expose to sunlight, high and low temperatures

DESCRIPTION

INSTRUCTIONS: A rich color lipstick that moistly adheres to lips.

Directions: Twist to dispense makeup and apply evenly to lips